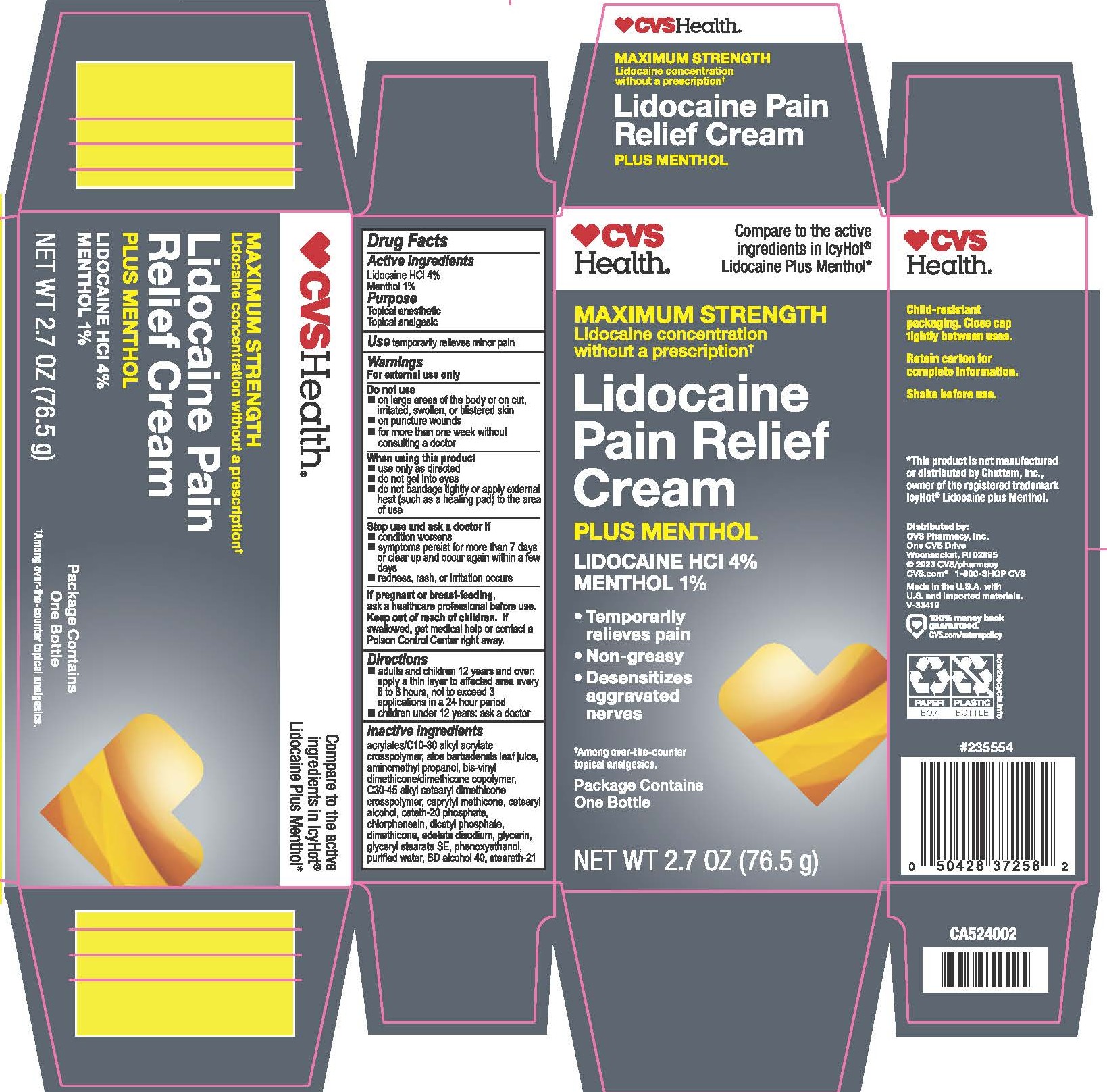 DRUG LABEL: CVS Health Maximum Strength Lidocaine Pain Relief Cream Plus Menthol
NDC: 59779-910 | Form: CREAM
Manufacturer: CVS Pharmacy
Category: otc | Type: HUMAN OTC DRUG LABEL
Date: 20260121

ACTIVE INGREDIENTS: LIDOCAINE HYDROCHLORIDE 40 mg/1 g; LEVOMENTHOL 10 mg/1 g
INACTIVE INGREDIENTS: CARBOMER INTERPOLYMER TYPE A (ALLYL SUCROSE CROSSLINKED); ALOE VERA LEAF; AMINOMETHYLPROPANOL; DIMETHICONE/VINYL DIMETHICONE CROSSPOLYMER (SOFT PARTICLE); C30-45 ALKYL METHICONE; CAPRYLYL TRISILOXANE; CETOSTEARYL ALCOHOL; CETETH-20 PHOSPHATE; CHLORPHENESIN; DIHEXADECYL PHOSPHATE; DIMETHICONE; EDETATE DISODIUM; GLYCERIN; GLYCERYL STEARATE SE; PHENOXYETHANOL; WATER; ALCOHOL; STEARETH-21

Drug Facts - CVS Health Maximum Strength Lidocaine Pain Relief Cream Plus Menthol

Active ingredients

Lidocaine HCl 4%

Menthol 1%

Purpose

Lidocaine HCl - Topical anesthetic

Menthol – Topical analgesic

Uses

temporarily relieves minor pain

Warnings

For external use only

Do not use

- on large areas of the body or on cut, irritated, swollen, or blistered skin
- on puncture wounds
- for more than one week without consulting a doctor

When using this product

- use only as directed
- do not get into eyes
- do not bandage tightly or apply external heat (such as a heating pad) to the area of use

Stop use and ask a doctor if

- condition worsens
- symptoms persist for more than 7 days or clear up and occur again within a few days
- redness, rash, or irritation occurs

If pregnant or breast-feeding,

ask a health professional before use.

Keep out of reach of children.

If swallowed, get medical help or contact a Poison Control Center right away.

Directions

- adults and children 12 years and over: apply a thin layer to affected area every 6 to 8 hours, not to exceed 3 applications in a 24 hour period
- children under 12 years: ask a doctor

Inactive ingredients

acrylates/C10-30 alkyl acrylate crosspolymer, aloe barbadensis leaf juice, aminomethyl propanol, bis-vinyl dimethicone/dimethicone copolymer, C30-45 alkyl cetearyl dimethicone crosspolymer, caprylyl methicone, cetearyl alcohol, ceteth-20 phosphate, chlorphenesin, dicetyl phosphate, dimethicone, edetate disodium, glycerin, glyceryl stearate SE, phenoxyethanol, purified water, SD alcohol 40, steareth-21